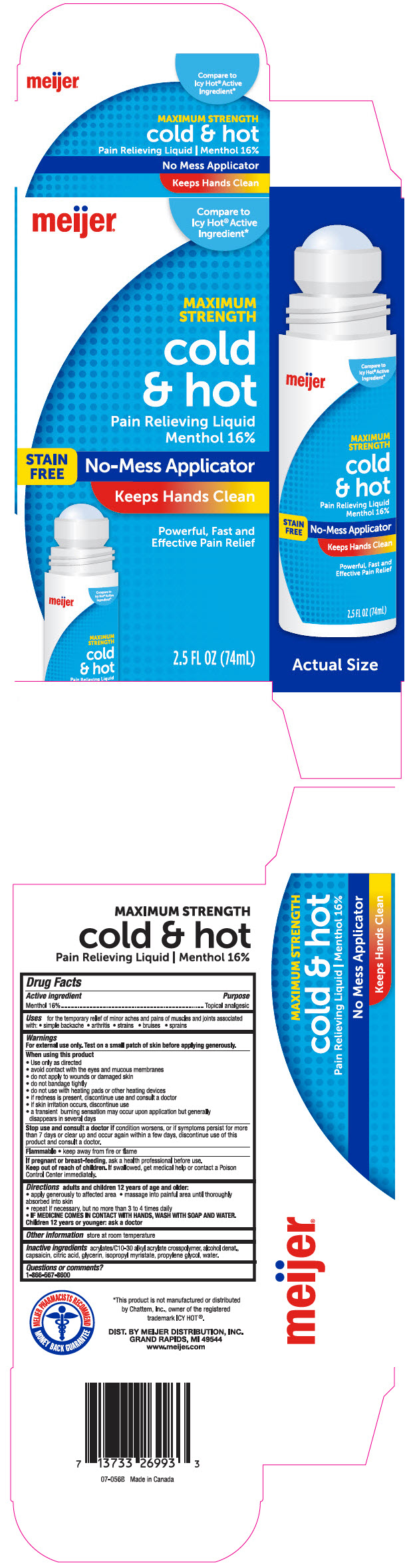 DRUG LABEL: Meijer Maximum Strength Pain Relieving
NDC: 41250-350 | Form: LIQUID
Manufacturer: Meijer Distribution, Inc
Category: otc | Type: HUMAN OTC DRUG LABEL
Date: 20241106

ACTIVE INGREDIENTS: Menthol, Unspecified Form 160 mg/1 mL
INACTIVE INGREDIENTS: Carbomer Interpolymer Type A (Allyl Sucrose Crosslinked); Alcohol; Capsaicin; Citric Acid Monohydrate; Glycerin; Isopropyl Myristate; Propylene Glycol; Water

Meijer® Maximum Strength Pain Relieving Liquid
Topical Analgesic

Drug Facts

Active ingredients

Menthol 16%

Purpose

Topical analgesic

Uses

for the temporary relief of minor aches and pains of muscles and joints associated with:

- simple backache
- arthritis
- strains
- bruises
- sprains

Warnings

For external use only. Test on a small patch of skin before applying generously.

When using this product

- use only as directed
- avoid contact with the eyes and mucous membranes
- do not apply to wounds or damaged skin
- do not bandage tightly
- do not use with heating pads or other heating devices
- if redness is present, discontinue use and consult a doctor
- if skin irritation occurs, discontinue use
- a transient burning sensation may occur upon application but generally disappears in several days

Stop use and consult a doctor if condition worsens, or if symptoms persist for more than 7 days or clear up and occur again within a few days, discontinue use of this product and consult a doctor.

Flammable

- keep away from fire or flame

PREGNANCY OR BREAST FEEDING

If pregnant or breast-feeding, ask a health professional before use.

Keep out of reach of children. If swallowed, get medical help or contact a Poison Control Center immediately.

Directions

adults and children 12 years of age and older:

- apply generously to affected area
- massage into painful area until thoroughly absorbed into skin
- repeat if necessary, but not more than 3 to 4 times daily
- IF MEDICINE COMES IN CONTACT WITH HANDS, WASH WITH SOAP AND WATER.

Children 12 years or younger: ask a doctor

Other information

store at room temperature

Inactive ingredients

acrylates/C10-30 alkyl acrylate crosspolymer, alcohol denat., capsaicin, citric acid, glycerin, isopropyl myristate, propylene glycol, water.

Questions or comments?

1-866-567-8600

DIST. BY MEIJER DISTRIBUTION, INC.
GRAND RAPIDS, MI 49544

PRINCIPAL DISPLAY PANEL - 74 mL Bottle Carton

meijer®

Compare to
Icy Hot® Active
Ingredient*

MAXIMUM
STRENGTH

cold
& hot

Pain Relieving Liquid
Menthol 16%

STAIN
FREE

No-Mess Applicator

Keeps Hands Clean

Powerful, Fast and
Effective Pain Relief

2.5 FL OZ (74mL)